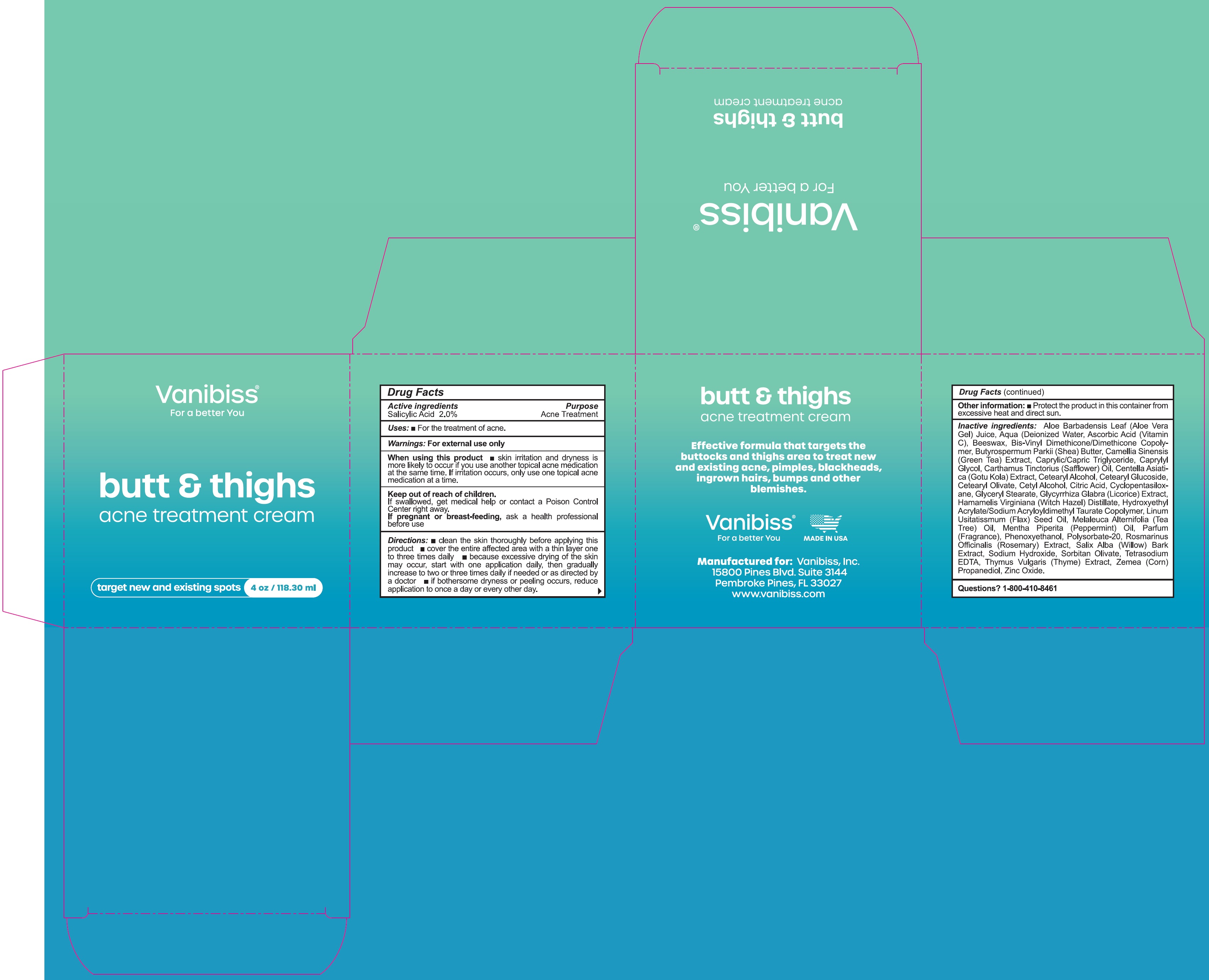 DRUG LABEL: VANIBISS BUTT and THIGHS Acne Treatment Cream
NDC: 81890-192 | Form: CREAM
Manufacturer: Vanibiss Inc
Category: otc | Type: HUMAN OTC DRUG LABEL
Date: 20231111

ACTIVE INGREDIENTS: SALICYLIC ACID 20 mg/1 mL
INACTIVE INGREDIENTS: ALOE VERA LEAF; WATER; ASCORBIC ACID; YELLOW WAX; SHEA BUTTER; GREEN TEA LEAF; MEDIUM-CHAIN TRIGLYCERIDES; CAPRYLYL GLYCOL; SAFFLOWER; CENTELLA ASIATICA LEAF; CETOSTEARYL ALCOHOL; CETEARYL GLUCOSIDE; CETEARYL OLIVATE; CETYL ALCOHOL; CITRIC ACID MONOHYDRATE; CYCLOMETHICONE 5; GLYCERYL MONOSTEARATE; GLYCYRRHIZA GLABRA; HAMAMELIS VIRGINIANA ROOT BARK/STEM BARK; LINSEED OIL; PEPPERMINT OIL; PHENOXYETHANOL; POLYSORBATE 20; ROSEMARY; SALIX ALBA BARK; SODIUM HYDROXIDE; SORBITAN OLIVATE; EDETATE SODIUM; THYME; CORN; ZINC OXIDE

VANIBISS BUTT & THIGHS Acne Treatment Cream

Active ingredients

Salicylic Acid 2.0%

Purpose

Acne Treatment

Uses

- For the treatment of acne.

Warnings:

For external use only

When using this product

- skin irritation and dryness is more likely to occur if you use another topical acne medication at the same time. If irritation occurs, only use one topical acne medication at a time.

Keep out of reach of children.

If swallowed, get medical help or contact a Poison Control Center right away.

If pregnant or breast-feeding,

ask a health professional before use

Directions:

- clean the skin thoroughly before applying this product
- cover the entire affected area with a thin layer one to three times daily
- because excessive drying of the skin may occur, start with one application daily, then gradually increase to two or three times daily, if needed or as directed by a doctor
- if bothersome dryness or peeling occurs, reduce application to once a day or every other day.

Other information:

- Protect the product in this container from excessive heat and direct sun.

Inactive ingredients:

Aloe Barbadensis Leaf (Aloe Vera Gel) Juice, Aqua (Deionized Water), Ascorbic Acid (Vitamin C), Beeswax, Bis-Vinyl Dimethicone/Dimethicone Copolymer, Butyrospermum Parkii (Shea) Butter, Camellia Sinensis (Green Tea) Extract, Caprylic/Capric Triglyceride, Caprylyl Glycol, Carthamus Tinctorius (Safflower) Oil, Centella Asiatica (Gotu Kola) Extarct, Cetearyl Alcohol, Cetearyl Glucoside, Cetearyl Olivate, Cetyl Alcohol, Citric Acid, Cyclopentasiloxane, Glyceryl Stearate, Glycyrrhiza Glabra (Licorice) Extract, Hamamelis Virginiana (Witch Hazel) Distillate, Hydroxyethyl Acrylate/Sodium (Flax) Seed Oil, Mentha Piperita (Peppermint) Oil, Parfum (Fragrance), Phenoxyethanol, Polysorbate-20, Rosmarinus Officinalis (Rosemary) Extarct, Salix Alba (Willow) Bark Extarct, Sodium Hydroxide, Sorbitan Olivate, Tetrasodium EDTA, Thymus Vulgaris (Thyme) Extarct, Zemea (Corn) propanediol, Zinc Oxide.

Questions?

1-800-410-8461